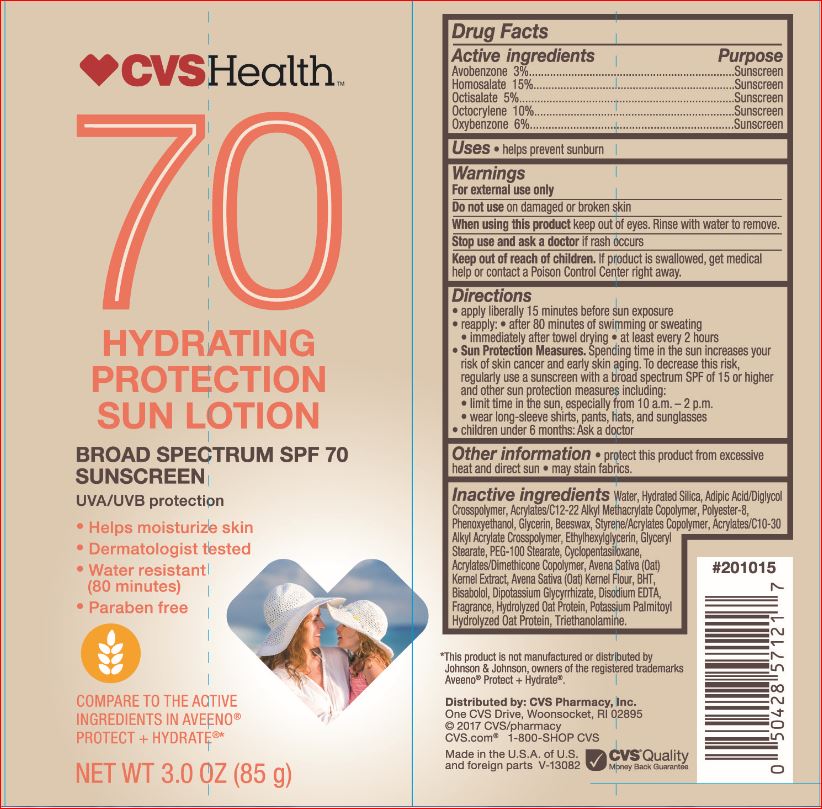 DRUG LABEL: Hydrating Protection Sunscreen
NDC: 69842-054 | Form: LOTION
Manufacturer: CVS
Category: otc | Type: HUMAN OTC DRUG LABEL
Date: 20171212

ACTIVE INGREDIENTS: Avobenzone 3 g/100 mL; Homosalate 15 g/100 mL; Octisalate 5 g/100 mL; Octocrylene 10 g/100 mL; Oxybenzone 6 g/100 mL
INACTIVE INGREDIENTS: CARBOMER INTERPOLYMER TYPE A (ALLYL SUCROSE CROSSLINKED); ADIPIC ACID/DIGLYCOL CROSSPOLYMER (20000 MPA.S); YELLOW WAX; BUTYLATED HYDROXYTOLUENE; LEVOMENOL; CYCLOMETHICONE 5; GLYCYRRHIZINATE DIPOTASSIUM; EDETATE DISODIUM; Ethylhexylglycerin; Glycerin; GLYCERYL MONOSTEARATE; Hydrated Silica; PEG-100 Stearate; Phenoxyethanol; POLYESTER-8 (1400 MW, CYANODIPHENYLPROPENOYL CAPPED); TROLAMINE; WATER; OAT; OATMEAL

Drug Facts

Active ingredients Purpose
Avobenzone 3%...................................................................Sunscreen
Homosalate 15%..................................................................Sunscreen
Octisalate 5%.......................................................................Sunscreen
Octocrylene 10%..................................................................Sunscreen
Oxybenzone 6%..................................................... .............Sunscreen

INDICATIONS AND USAGE

Uses • helps prevent sunburn

Warnings
For external use only
Do not use on damaged or broken skin
When using this product keep out of eyes. Rinse with water to remove.
Stop use and ask a doctor if rash occurs

Keep out of reach of children. If product is swallowed, get medical help or contact a Poison Control Center right away.

Directions
• apply liberally 15 minutes before sun exposure
• reapply: • after 80 minutes of swimming or sweating
• immediately after towel drying • at least every 2 hours
• Sun Protection Measures. Spending time in the sun increases your
risk of skin cancer and early skin aging. To decrease this risk,
regularly use a sunscreen with a broad spectrum SPF of 15 or higher
and other sun protection measures including:
• limit time in the sun, especially from 10 a.m. – 2 p.m.
• wear long-sleeve shirts, pants, hats, and sunglasses
• children under 6 months: Ask a doctor

Inactive ingredients

Acrylates/C10-30 Alkyl Acrylate
Crosspolymer, Acrylates/C12-22 Alkyl Methacrylate Copolymer,
Acrylates/Dimethicone Copolymer, Adipic Acid/Diglycol Crosspolymer, Avena
Sativa (Oat) Kernel Extract, Avena Sativa (Oat) Kernel
Flour, Beeswax, BHT, Bisabolol, Cyclopentasiloxane,
Dipotassium Glycyrrhizate, Disodium EDTA,
Ethylhexylglycerin, Fragrance, Glycerin, Glyceryl
Stearate, Hydrated Silica, Hydrolyzed Oat Protein,
PEG-100 Stearate, Phenoxyethanol, Polyester-8,
Potassium Palmitoyl Hydrolyzed Oat Protein,
Styrene/Acrylates Copolymer,Triethanolamine, Water